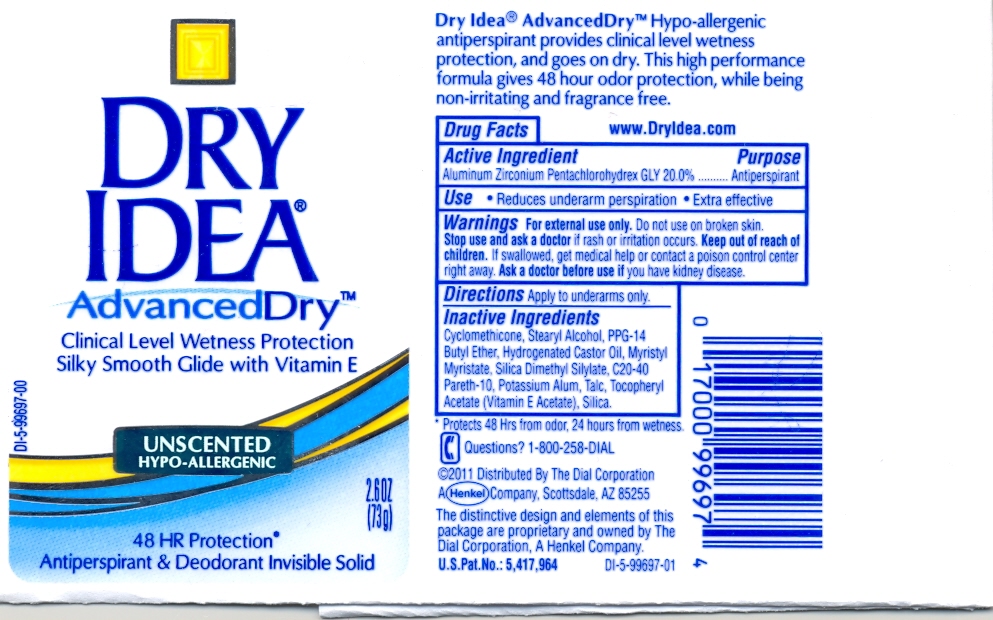 DRUG LABEL: Dry Idea A.Dry Antiperspirant Solid Unscented
NDC: 54340-969 | Form: STICK
Manufacturer: The Dial Corporation
Category: otc | Type: HUMAN OTC DRUG LABEL
Date: 20110211

ACTIVE INGREDIENTS: Aluminum Zirconium Pentachlorohydrex gly 14.6 g/73 g
INACTIVE INGREDIENTS: Stearyl Alcohol 11.68 g/73 g; PPG-14 Butyl Ether 7.30 g/73 g; Hydrogenated Castor Oil 2.080 g/73 g; SILICON DIOXIDE 2.065 g/73 g; MYRISTYL MYRISTATE 1.460 g/73 g; Talc 0.730 g/73 g; Potassium Alum 0.0730 g/73 g

Dry Idea AdvancedDry Clinical Wetness Protection Antiperspirant & Deodorant Invisible Solid Unscented

ACTIVE INGREDIENT

Aluminum Zirconium Pentachlorohydrex Gly 20.0%......Antiperspirant

PURPOSE

Reduces underarm perspiration - Extra effective

WARNINGS

For external use only. Do not use on broken skin.

Stop use and ask a doctor if rash or irritation occurs.

Keep out of reach of children.

GENERAL PRECAUTIONS

If swallowed, get medical help or contact a poison control center right away.

Ask a doctor before use if you have kidney disease.

DOSAGE AND ADMINISTRATION

Directions: Apply to underarms only.

INACTIVE INGREDIENT

Cyclomethicone, Stearyl Alcohol, PPG-14 Butyl Ether, Hydrogenated Castor Oil, Myristyl Myristate, Silica Dimethyl Silylate, C20-40 Pareth-10, Potassium Alum, Talc, Tocopheyl Acetate (Vitamin E Acetate), Silica.

INDICATIONS AND USAGE

Protects 48 Hrs from odor, 24 Hours from wetness.

Questions? 1-800-258-DIAL

HOW SUPPLIED

2011 Distributed by The Dial Corporation A Henkel Company, Scottsdale, AZ 85255.

The distinctive design and elements of this package are proprietary and owned by The Dial Corporation, A Henkel Company. U.S.Pat.No:5,417,964.